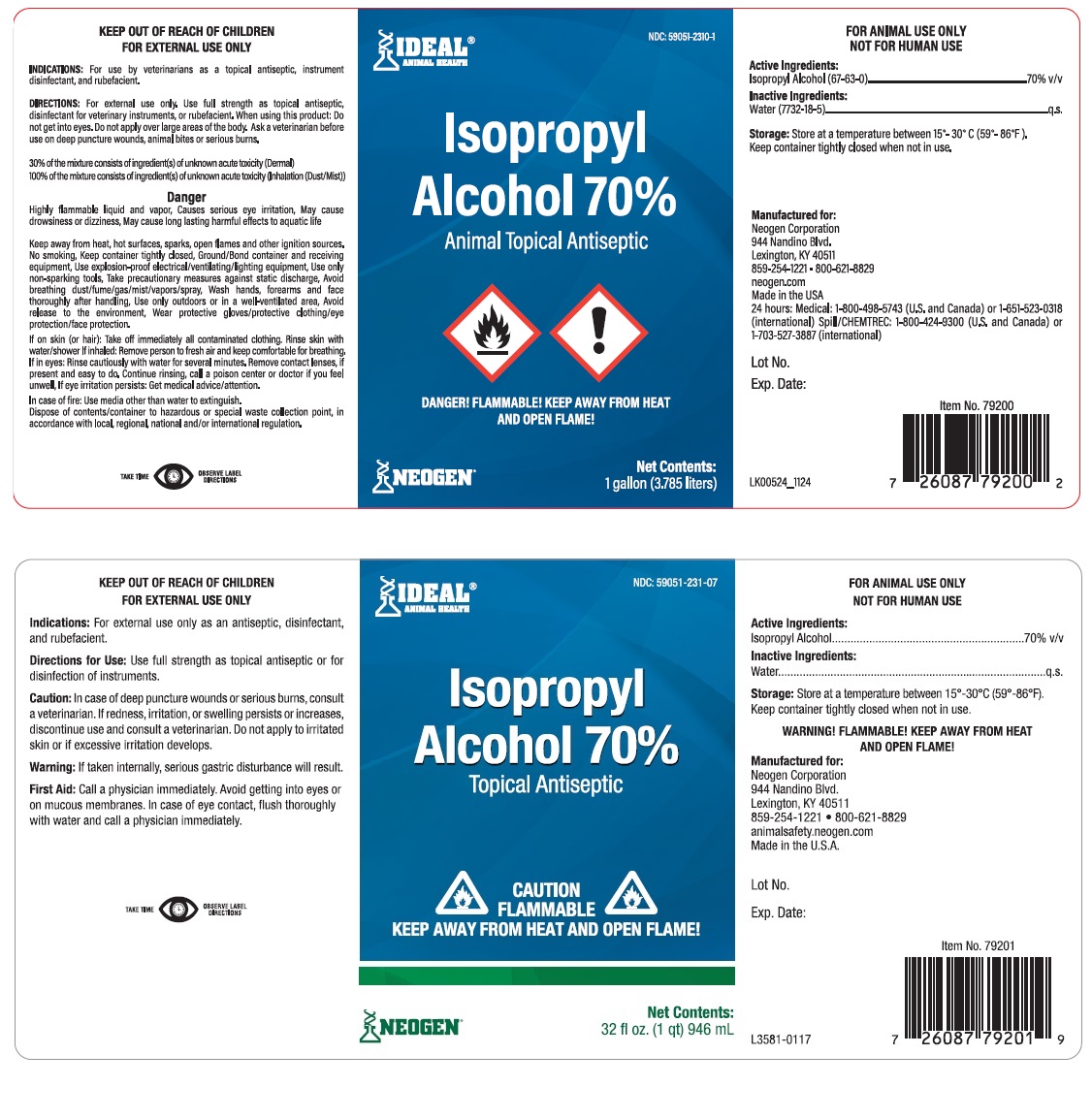 DRUG LABEL: Isopropyl Alcohol
NDC: 59051-2310 | Form: LIQUID
Manufacturer: Neogen Corp
Category: animal | Type: OTC ANIMAL DRUG LABEL
Date: 20251206

ACTIVE INGREDIENTS: ISOPROPYL ALCOHOL 70 L/100 L
INACTIVE INGREDIENTS: water 30 L/100 L

WARNINGS AND PRECAUTIONS

Isopropyl Alcohol 70%

Topical Antiseptic

FOR ANIMAL USE ONLY

NOT FOR HUMAN USE

Active Ingredient:

Isopropyl Alcohol (67-63-0)................................ 70% v/v

Inactive Ingredients:

Water (7732-18-5) ................................................. q.s

Storage: Store at a temperature between 15º-30ºC (59º-86ºF). Keep container tightly closed when not in use.

INDICATIONS: For use by veterinarians as a topical antiseptic, instrument disinfectant, and rubefacient.

DIRECTIONS: For external use only. Use full strength as topical antiseptic, disinfectant for veterinary instruments, or rubefacient. When using this product: Do not get into eyes. Do not apply over large areas of the body. Ask a veterinarian before use on deep puncture wounds, animal bites or serious burns.

30% of the mixture consisls of ingredient(s) of unknown acute toxicity (Demial)
100% of the mixture consisls of ingredient(s) of unknown acute toxicity (Inhalation (Dust/Mist))

Danger

Highly flammable liquid and vapor, Causes serious eye irritation, May cause drowsiness or dizziness, May cause long lasting harmful effects to aquatic life.

May be used for temporary relief of minor muscular aches or pain due to over-exertion and fatigue. Apply directly to affected area, wet thoroughly and massage briskly to stimulate circulation.

Keep away from heat, hot surfaces, sparks, open flames and other ignition sources. No smoking, Keep container tightly closed, Ground/Bond container and receiving equipment, Use explosion-proof electrical/ventilating/lighting equipment, Use only non-sparking tools, Take precautionary measures against static discharge, Avoid breathing dust/fume/gas/mist/vapors/spray, Wash hands, forearms and face
thoroughly after handling, Use only outdoors or in a well-ventilated area, Avoid release to the environment, Wear protective gloves/protective clothing/eye protection/face protection.

If on skin (or hair): Take off immediately all contaminated clothing. Rinse skin with water/shower If inhaled: Remove person to fresh air and keep comfortable for breathing. If in eyes: Rinse cautiously with water for several minutes. Remove contact lenses, if present and easy to do. Continue rinsing, call a poison center or doctor if you feel unwell, If eye irritation persists: Get medical advice/attention.

In case of fire: Use media other than water to extinguish.

Dispose of contents/container to hazardous or special waste collection point, in accordance with local, regional, national and/or international regulation.

TAKET OBSERVE LABEL DIRECTIONS.

Manufactured for:

Neogen Corporation
944 Nandino Blvd.
Lexington, KY 40511
859-254-1221 • 800-621-8829
neogen.com
Made in the USA
24 hours: Medical: 1-800-498-5743 (U.S. and Canada) or 1-651-523-0318
(international) Spill/CHEMTREC: 1-800-424-9300 (U.S. and Canada) or 1-703-527-3887 (international)